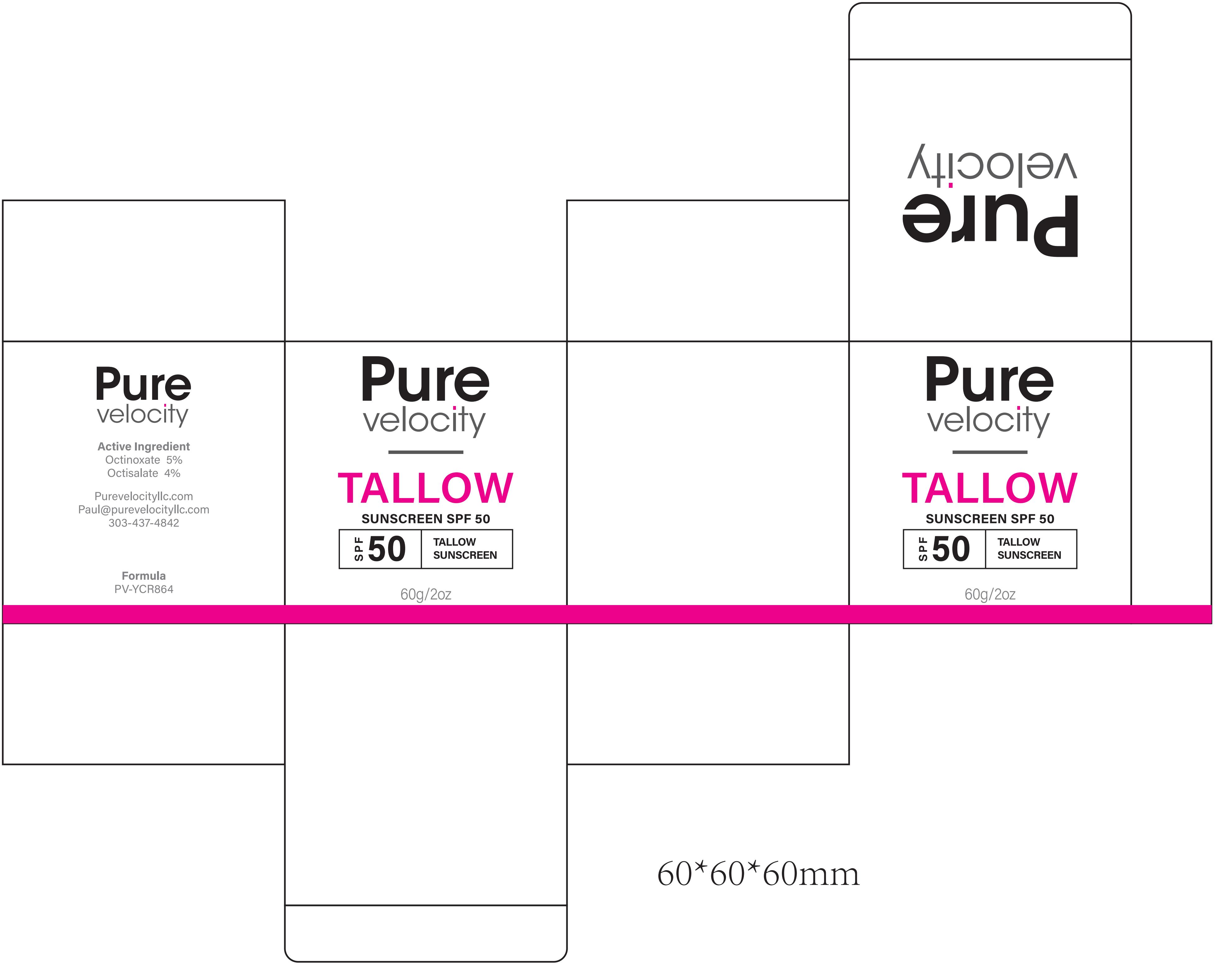 DRUG LABEL: Pure velocity TALLOW SUNSCREEN SPF 50
NDC: 60771-0036 | Form: CREAM
Manufacturer: Guangzhou Haishi Biological Technology Co., Ltd.
Category: otc | Type: HUMAN OTC DRUG LABEL
Date: 20250930

ACTIVE INGREDIENTS: ETHYLHEXYL SALICYLATE 2.4 g/100 g; ETHYLHEXYL METHOXYCINNAMATE 3 g/100 g
INACTIVE INGREDIENTS: ADEPS BOVIS; GLYCERIN; ALUMINUM DICHLOROHYDREX PROPYLENE GLYCOL; SAURURUS CHINENSIS FLOWER; WATER

Active Ingredients

ETHYLHEXYL METHOXYCINNAMATE
ETHYLHEXYL SALICYLATE

Purpose

SUNSCREEN

Uses

If used as directed with other sun protection measures(see Directions)，
decreases the risk of skin cancer and early skin aging caused by the sun.

Warnings

For external use only

Stop Use

Rinse with wate to remove.
Stop use and ask doctor if rash occurs.

Do not use on damaged or broken skin.

When Using

When using this product keep out of eyes.

Keep Out Of Reach Of Children

Dosage & administration

Squeeze out an appropriate amount of Sunscreen and spread evenly on skin.

Inactive ingredients

WATER
ADEPS BOVIS
PROPYLENE GLYCOL
GLYCERIN
SAURURUS CHINENSIS LEAF/ROOT EXTRACT
CETEARYL ALCOHOL
CETETH-2
TOCOPHERYL ACETATE
DIMETHICONE
CETEARYL GLUCOSIDE
CETETH-21
TARAXACUM OFFICINALE (Dandelion) Leaf Extract
PHENOXYETHANOL
ALLANTOIN
BISABOLOL
CARBOMER
TRIETHANOLAMINE
SODIUM HYALURONATE
ETHYLHEXYLGLYCERIN
STEPHANIA TETRANDRA EXTRACT